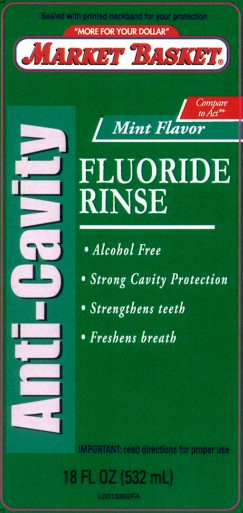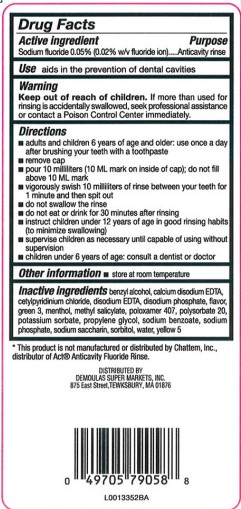 DRUG LABEL: Anticavity Fluoride Rinse
NDC: 53942-213 | Form: MOUTHWASH
Manufacturer: Demoulas Super Markets, Inc
Category: otc | Type: HUMAN OTC DRUG LABEL
Date: 20260203

ACTIVE INGREDIENTS: SODIUM FLUORIDE 0.2 mg/1 mL
INACTIVE INGREDIENTS: EDETATE CALCIUM DISODIUM ANHYDROUS; EDETATE DISODIUM ANHYDROUS; SODIUM BENZOATE; POTASSIUM SORBATE; BENZYL ALCOHOL; FD&C GREEN NO. 3; FD&C YELLOW NO. 5; WATER; SORBITOL; MENTHOL; METHYL SALICYLATE; CETYLPYRIDINIUM CHLORIDE; SACCHARIN SODIUM; POLOXAMER 407; POLYSORBATE 20; PROPYLENE GLYCOL; SODIUM PHOSPHATE; SODIUM PHOSPHATE, DIBASIC, ANHYDROUS

Market Basket 213.002/213AE rev 2
Anticavity Fluoride Rinse, Mint

Active ingredient

Sodium fluoride 0.05% (0.02% w/v fluoride ion)

Purpose

Anticavity rinse

Use

aids in the prevention of dental cavities

Warning

for this product

Keep out of reach of children.

If more than used for rinsing is accidentally swallowed, seek professional assistance or contact a Poison Control Center immediately.

Directiions

- adults and children 6 years of age and older: use once a day after brushing your teeth with a toothpaste
- remove cap
- pour 10 milliliters (10 mL mark on the inside of cap); do not fill above the 10 mL mark
- vigorously swish 10 milliliters of rinse between your teeth for 1 minute then spit out
- do not swallow the rinse
- do not eat or drink for 30 minutes after rinsing
- instruct children under 12 years of age in good rinsing habits (to minimize swallowing)
- supervise children as necessary until capable of using without supervision
- children under 6 years of age: consult a dentist or doctor

Other information

- store at room temperature

Inactive ingredients

benzyl alcohol, calcium disodium EDTA, cetylpyridinium chloride, disodium EDTA, disodium phosphate, flavor, green 3, menthol, methyl salicylate, poloxamer 407, polysorbate 20, potassium sorbate, propylene glycol, sodium benzoate, sodium phosphate, sodium saccharin, sorbitol, water, yellow 5

ADVERSE REACTION

*This product is not manufactured or distributed by Chattem, Inc., distributor of Act® Anticavity Fluoride Rinse

DISTRIBUTED BY:

Demoulas Super Markets, Inc.

875 East Street, Tewksbury, MA 01876

principal display panel

Sealed With Printed Necband For Your Protection

"MORE FOR YOUR DOLLAR"

Market Basket®

COMPARE TO ACT®*

Mint Flavor

ANTI-CAVITY

Fluoride Rinse

- Alcohol free
- Strong cavity protection
- Strengthens teeth
- Freshens breath

IMPORTANT: read directions for proper use.

18 FL OZ (532 mL)